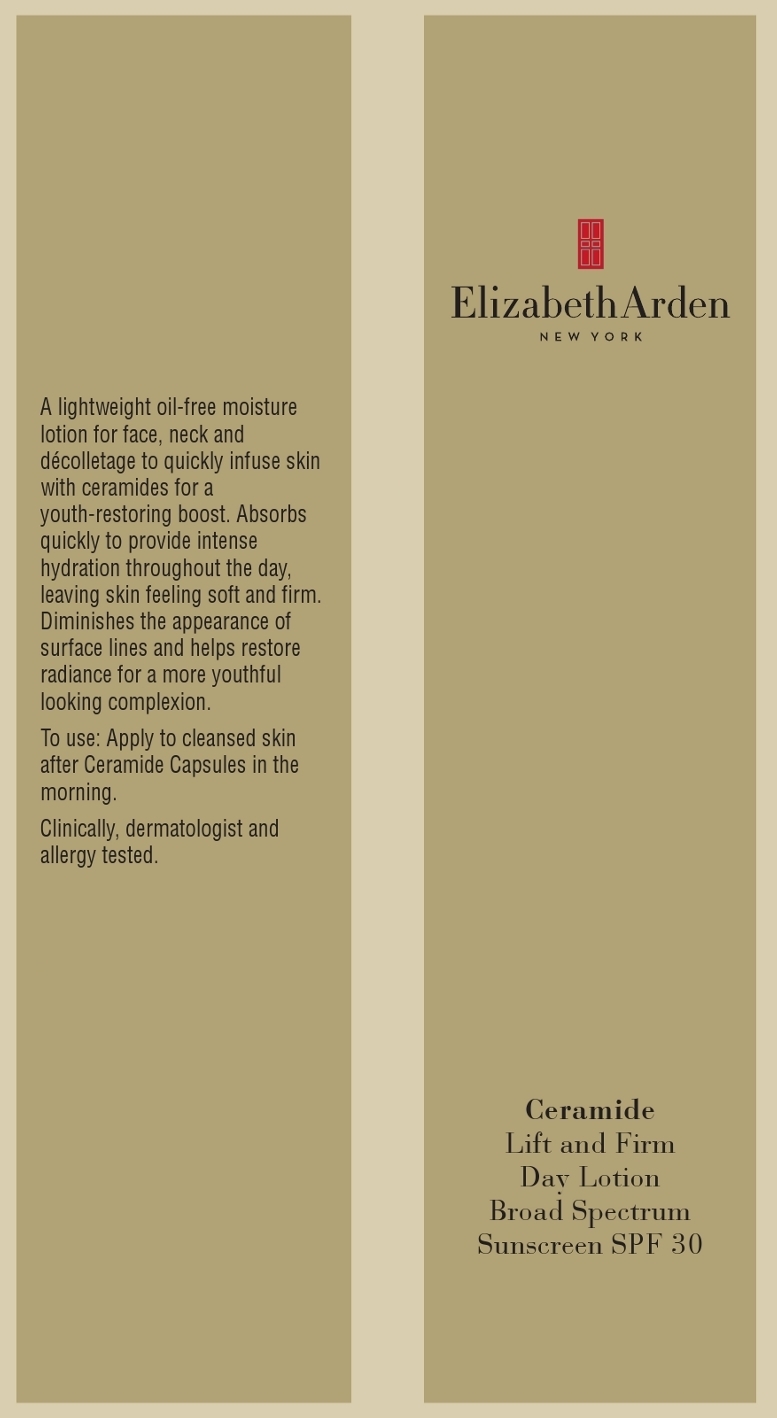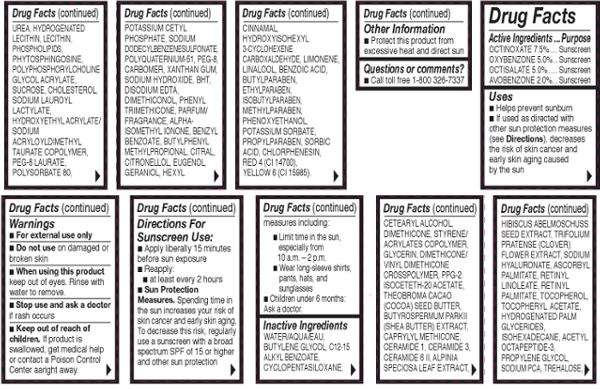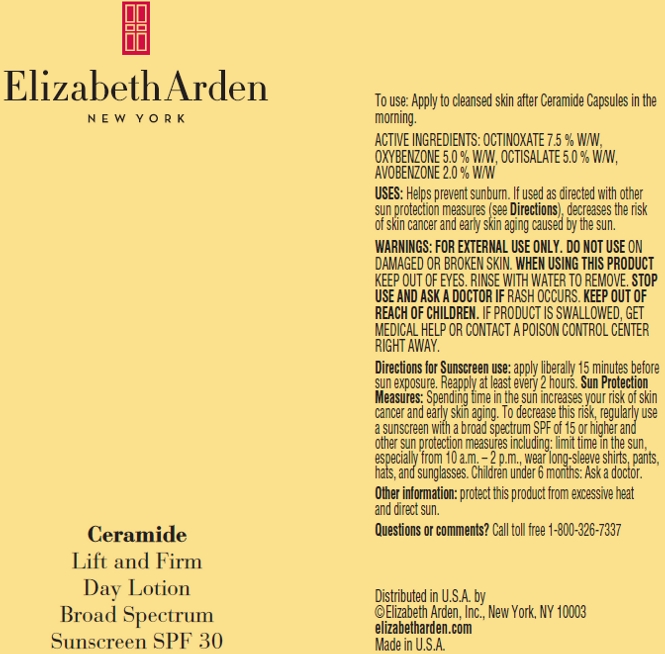 DRUG LABEL: Ceramide Lift And Firm Day Broad Spectrum Sunscreen SPF 30
NDC: 67938-0802 | Form: LOTION
Manufacturer: Elizabeth Arden, Inc
Category: otc | Type: HUMAN OTC DRUG LABEL
Date: 20130419

ACTIVE INGREDIENTS: OCTINOXATE 3.75 g/50 g; OXYBENZONE 2.5 g/50 g; OCTISALATE 2.5 g/50 g; AVOBENZONE 1 g/50 g
INACTIVE INGREDIENTS: WATER; BUTYLENE GLYCOL; ALKYL (C12-15) BENZOATE; CYCLOMETHICONE 5; CETOSTEARYL ALCOHOL; DIMETHICONE; GLYCERIN; COCOA BUTTER; SHEA BUTTER; CAPRYLYL TRISILOXANE; CERAMIDE 1; CERAMIDE 3; CERAMIDE 6 II; ALPINIA ZERUMBET LEAF; ABELMOSCHUS MOSCHATUS SEED; TRIFOLIUM PRATENSE FLOWER; HYALURONATE SODIUM; ASCORBYL PALMITATE; RETINYL LINOLEATE; VITAMIN A PALMITATE; TOCOPHEROL; .ALPHA.-TOCOPHEROL ACETATE; HYDROGENATED PALM GLYCERIDES; ISOHEXADECANE; PROPYLENE GLYCOL; SODIUM PYRROLIDONE CARBOXYLATE; TREHALOSE; UREA; HYDROGENATED SOYBEAN LECITHIN; EGG PHOSPHOLIPIDS; OMEGA-3 FATTY ACIDS; PHYTOSPHINGOSINE; SUCROSE; CHOLESTEROL; SODIUM LAUROYL LACTYLATE; HYDROXYETHYL ACRYLATE/SODIUM ACRYLOYLDIMETHYL TAURATE COPOLYMER (45000 MPA.S AT 1%); PEG-8 LAURATE; POLYSORBATE 80; POTASSIUM CETYL PHOSPHATE; SODIUM DODECYLBENZENESULFONATE; XANTHAN GUM; SODIUM HYDROXIDE; BUTYLATED HYDROXYTOLUENE; PHENYL TRIMETHICONE; ISOMETHYL-.ALPHA.-IONONE; BENZYL BENZOATE; BUTYLPHENYL METHYLPROPIONAL; CITRAL; EUGENOL; GERANIOL; .ALPHA.-HEXYLCINNAMALDEHYDE; HYDROXYISOHEXYL 3-CYCLOHEXENE CARBOXALDEHYDE; BENZOIC ACID; BUTYLPARABEN; ETHYLPARABEN; ISOBUTYLPARABEN; METHYLPARABEN; PHENOXYETHANOL; POTASSIUM SORBATE; PROPYLPARABEN; SORBIC ACID; CHLORPHENESIN; FD&C RED NO. 4; FD&C YELLOW NO. 6

BB0802

DESCRIPTION

A lightweight, oil-free lotion for face, neck, and decolletage to quickly infuse skin with ceramides for a youth-restoring boost. Absorbs quickly to provide intense hydration throughout the day, leaving skin feeling soft and firm. Diminished the appearance of surface lines and helps restore radiance for a more youthful looking complexion.

INDICATIONS AND USAGE

To Use: Apply to cleansed skin after Ceramide Capsules in the morning.

Directions for Sunscreen Use: Apply liberally 15 minutes before sun exposure. Reapply at least every 2 hours.

Sun Protection Measures: Spending time in the sun increases your risk of skin cancer and early skin aging. To decrease this risk, regularly use a sunscreen with a broad spectrum SPF of 15 or higher and other sun protection measures including: Limit time in the sun, especially from 10 a.m. - 2 p.m.. Wear long-sleeve shirts, pants, hats, and sunglesses.

WARNINGS

For external use only.

Do not use on damaged or broken skin.

When using this product, keep out of eyes. Rinse with water to remove.

Stop use and ask a doctor if rash occurs.

OTC - ACTIVE INGREDIENT

Active Ingredients: Octinoxate 7.5%, Oxybenzone 5.0%, Octisalate 5.0%, Avobenzone 2.0%.

INACTIVE INGREDIENT

Other Ingredients: Water/Aqua/Eau, Butylene Glycol, C12-15 Alkyl Benzoate, Cyclopentasiloxane, Cetearyl Alcohol, Dimethicone, Styrene/Acrylates Copolymer, Glycerin, Dimethicone/Vinyl Dimethicone Crosspolymer, PPG-2 Isoceteth-20 Acetate, Theobroma Cacao (Cocoa) Seed Butter, Butyrospermum Parkii (Shea Butter) Extract, Caprylyl Methicone, Ceramide 1, Ceramide 3, Ceramide 6 II, Alpinia Speciosa Leaf Extract, Hibiscus Abeloschuss Seed Extract, Trifolium Pratense (Clover) Flower Extract, Sodium Hyaluronate, Ascorbyl Palmitate, Retinyl Linoleate, Retinyl Palmitate, Tocopherol, Tocopheryl Acetate, Hydrogenated Lecithin, Lecithin, Phospholipids, Phytosphingosine, Polyphosphorylcholine Glycol Acrylate, Sucrose, Cholesterol, Sodium Lauroyl Lactylate, Hydroxyethyl Acrylate/Sodium Acryloyldimethyl Taurate Copolymer, PEG-8 Laurate, Polysorbate 80, Potassium Cetyl Phosphate, Sodium Dodecylbenzenesulfonate, Polyquaternium-51, PEG-8, Carbomer, Xanthan Gum, Sodium Hydroxide, BHT, Disodium EDTA, Dimethiconol, Phenyl Trimethicone, Parfum/Fragrance, Alpha-Isomethyl Ionone, Benzyl Benzoate, Butylphenyl Methylpropional Citral, Citronellol, Eugenol, Geraniol, Hexyl Cinnamai, Hydroxyisohexyl 3-Cyclohexene, Carboxaldehyde Limonene, Linalool, Benzoic Acid, Butylparaben, Ethylparaben, Isobutylparaben, Methylparaben, Phenoxyethanol, Potassium Sorbate, Propylparaben, Sorbic Acid, Chlorphenesin, Red 4 (CI 14700), Yellow 6 (CI 15985).

DOSAGE & ADMINISTRATION

Apply to skin.

OTC - KEEP OUT OF REACH OF CHILDREN

Keep out of reach of children. If product is swallowed, get medical help or contact a Poison Control center immediately.

OTC - PURPOSE

Provides SPF 30 sun protection.

OTC - WHEN USING

Keep out of eyes.